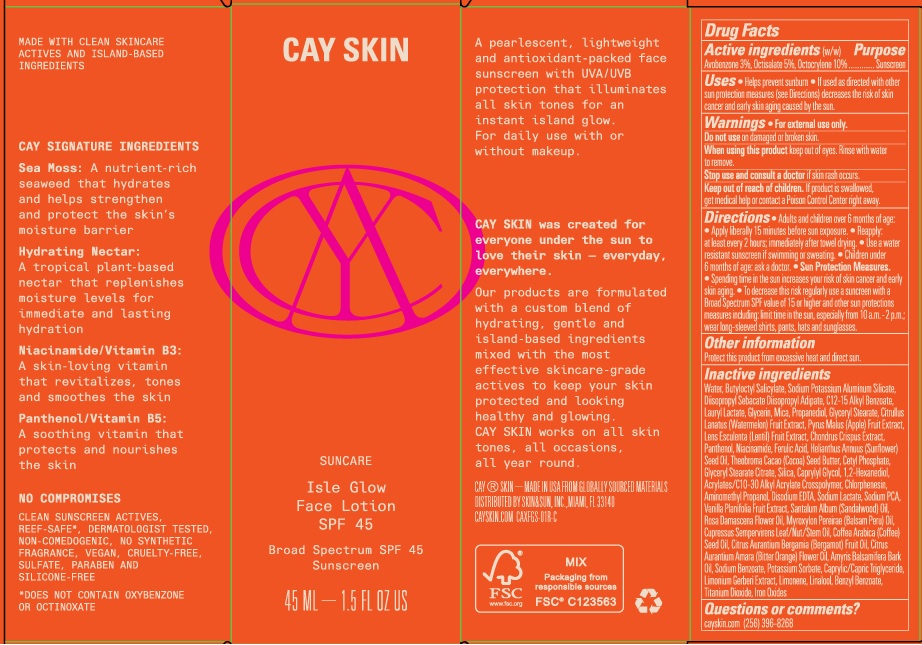 DRUG LABEL: Cay Skin Isle Glow Face SPF 45
NDC: 82657-002 | Form: LOTION
Manufacturer: Cay Skin, Inc.
Category: otc | Type: HUMAN OTC DRUG LABEL
Date: 20241205

ACTIVE INGREDIENTS: OCTOCRYLENE 100 mg/1 mL; AVOBENZONE 30 mg/1 mL; OCTISALATE 50 mg/1 mL
INACTIVE INGREDIENTS: LINALOOL, (+/-)-; TITANIUM DIOXIDE; CHONDRUS CRISPUS; PANTHENOL; NIACINAMIDE; SUNFLOWER OIL; COCOA BUTTER; CETYL PHOSPHATE; SILICON DIOXIDE; CARBOMER INTERPOLYMER TYPE A (55000 CPS); CHLORPHENESIN; FERRIC OXIDE RED; FERRIC OXIDE YELLOW; LIMONENE, (+/-)-; 1,2-HEXANEDIOL; EDETATE DISODIUM ANHYDROUS; SODIUM LACTATE; SANDALWOOD OIL; ROSA DAMASCENA FLOWER OIL; POTASSIUM SORBATE; MEDIUM-CHAIN TRIGLYCERIDES; LIMONIUM GERBERI WHOLE; BENZYL BENZOATE; FERROSOFERRIC OXIDE; SODIUM PYRROLIDONE CARBOXYLATE; VANILLA; AMYRIS BALSAMIFERA OIL; BALSAM PERU OIL; ARABICA COFFEE OIL; BERGAMOT OIL; BITTER ORANGE OIL; CUPRESSUS SEMPERVIRENS WHOLE; SODIUM BENZOATE; LAURYL LACTATE; GLYCERIN; DIISOPROPYL ADIPATE; WATER; BUTYLOCTYL SALICYLATE; DIISOPROPYL SEBACATE; ALKYL (C12-15) BENZOATE; GLYCERYL STEARATE CITRATE; MICA; PROPANEDIOL; APPLE; CAPRYLYL GLYCOL; AMINOMETHYLPROPANOL; FERULIC ACID; GLYCERYL MONOSTEARATE; WATERMELON; LENTIL

Cay Skin Isle Glow Face Lotion SPF 45

Active ingredients

Avobenzone 3%, Octisalate 5%, Octocrylene 10%

Purpose

Sunscreen

Uses

- Helps prevent sunburn
- If used as directed with other sun protection measures (see Directions) decreases the risk of skin cancer and early skin aging caused by the sun.

Warnings

For external use only.

Do not use

on damaged or broken skin.

When using this product

keep out of eyes. Rinse with water to remove.

Stop use and consult a doctor

if skin rash occurs.

Keep out of reach of children.

If product is swallowed, get medical help or contact a Poison Control Center right away.

Directions

- Adults and children over 6 months of age:
- Apply liberally 15 minutes before sun exposure.
- Reapply: at least every 2 hours; immediately after towel drying.
- Use a water resistant sunscreen if swimming or sweating.
- Children under 6 months of age: ask a doctor.
- Sun Protection Measures.
- Spending time in the sun increases your risk of skin cancer and early skin aging.
- To decrease this risk regularly use a sunscreen with a Broad Spectrum SPF value of 15 or higher and other sun protection measures including: limit time in the sun, especially from 10 a.m. - 2 p.m.; wear long-sleeved shirts, pants, hats and sunglasses.

Other information

Protect this product from excessive heat and direct sun.

Inactive ingredients

Water, Butyloctyl Salicylate, Sodium Potassium Aluminum Silicate, Diisopropyl Sebacate Diisopropyl Adipate, C12-15 Alkyl Benzoate, Lauryl Lactate, Glycerin, Mica, Propanediol, Glyceryl Stearate, Citrullus Lanatus (Watermelon) Fruit Extract, Pyrus Malus (Apple) Fruit Extract, Lens Esculents (Lentil) Fruit Extract, Chondrus Crispus Extract, Panthenol, Niacinamide, Ferulic Add, Helianthus Annuus (Sunflower) Seed Oil, Theobroma Cacao (Cocoa) Seed Butter, Cetyl Phosphate, Glyceryl Stearate Citrate, Silica, Caprylyl Glycol, 1,2-Hexanediol, Acrylates/C10-30 Alkyl Acrylate Crosspolymer, Chlorphenesin, Aminomethyl Propanol, Disodium EDTA, Sodium Lactate, Sodium PCA, Vanilla Planifolia Fruit Extract, Santalum Album (Sandalwood) Oi, Rosa Damascena Flower Oil, Myroxylon Pereirae (Balsam Peru) Oil, Cupressus Sempervirens Leaf/Nut/Stem Oil, Coffea Arabica (Coffee) Seed Oil, Citrus Aurantium Bergamia (Bergamot) Fruit Oil, Citrus Aurantium Amara (Bitter Orange) Flower Oil, Amyris Balsamifera Bark Oil, Sodium Benzoate, Potassium Sorbate, Caprylic/Capric Triglyceride, Limonium Gerberi Extract, Limonene, Linalool, Benzyl Benzoate, Titanium Dioxide, Iron Oxides

Questions or comments?

cayskin.com (256) 396-8268